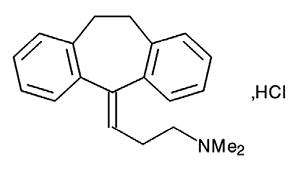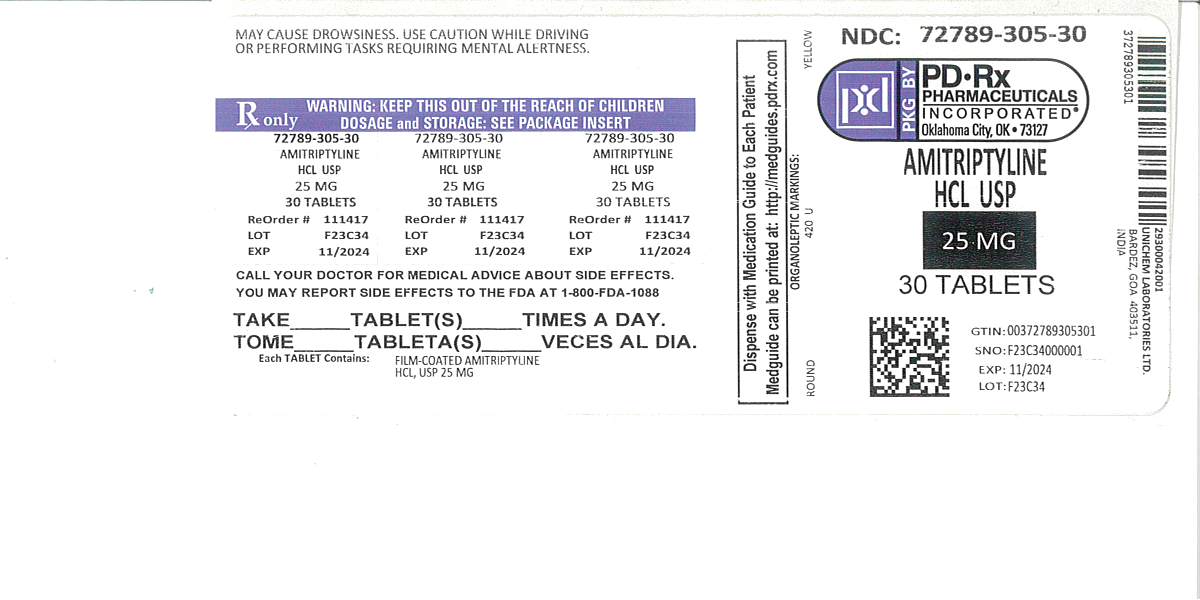 DRUG LABEL: Amitriptyline Hydrochloride
NDC: 72789-305 | Form: TABLET, FILM COATED
Manufacturer: PD-Rx Pharmaceuticals, Inc.
Category: prescription | Type: HUMAN PRESCRIPTION DRUG LABEL
Date: 20260226

ACTIVE INGREDIENTS: AMITRIPTYLINE HYDROCHLORIDE 25 mg/1 1
INACTIVE INGREDIENTS: CROSCARMELLOSE SODIUM; FERRIC OXIDE YELLOW; HYDROXYPROPYL CELLULOSE (110000 WAMW); HYPROMELLOSE 2910 (6 MPA.S); LACTOSE MONOHYDRATE; MAGNESIUM STEARATE; MICROCRYSTALLINE CELLULOSE; POLYETHYLENE GLYCOL 400; TITANIUM DIOXIDE

Amitriptyline Hydrochloride Tablets, USP
Rx Only

BOXED WARNING

Suicidality and Antidepressant Drugs :

Antidepressants increased the risk compared to placebo of suicidal thinking and behavior (suicidality) in children, adolescents, and young adults in short-term studies of major depressive disorder (MDD) and other psychiatric disorders. Anyone considering the use of amitriptyline hydrochloride tablets or any other antidepressant in a child, adolescent, or young adult must balance this risk with the clinical need. Short-term studies did not show an increase in the risk of suicidality with antidepressants compared to placebo in adults beyond age 24; there was a reduction in risk with antidepressants compared to placebo in adults aged 65 and older. Depression and certain other psychiatric disorders are themselves associated with increases in the risk of suicide. Patients of all ages who are started on antidepressant therapy should be monitored appropriately and observed closely for clinical worsening, suicidality, or unusual changes in behavior. Families and caregivers should be advised of the need for close observation and communication with the prescriber. Amitriptyline hydrochloride tablets are not approved for use in pediatric patients (see WARNINGS: Clinical Worsening and Suicide Risk, PRECAUTIONS: Information for Patients, and PRECAUTIONS: Pediatric Use).

DESCRIPTION

Amitriptyline hydrochloride, USP, a dibenzocycloheptadiene derivative, is a white, or practically white, odorless, crystalline compound which is freely soluble in water and alcohol.

It is designated chemically as 10,11-Dihydro-N,N-dimethyl-5 H-dibenzo[a, d] cycloheptene-Δ^5, γ-propylamine hydrochloride. It has the following structural formula:

C20H23N.HCl

M.W. 313.90

Each tablet for oral administration contains 10, 25, 50, 75, 100, or 150 mg amitriptyline hydrochloride, USP. Inactive ingredients include lactose monohydrate, microcrystalline cellulose, croscarmellose sodium, hydroxypropyl cellulose, magnesium stearate, hypromellose, titanium dioxide and polyethylene glycol. In addition, the following product specific coloring agents are included:

10 mg-D&C Red #27 Phloxine Aluminum Lake, D&C Yellow #10 Aluminum Lake and FD&C Blue #1 Aluminum Lake;

25 mg-Yellow iron oxide;

50 mg-D&C Yellow #10 Aluminum Lake, FD&C Red #40 Aluminum Lake and FD&C Blue #2 Aluminum Lake;

75 mg-Yellow iron oxide;

100 mg-D&C Yellow #10 Aluminum Lake and D&C Red #30 Aluminum Lake;

150 mg-Yellow iron oxide, Black iron oxide, D&C Yellow #10 Aluminum Lake and FD&C Blue #1 Aluminum Lake.

CLINICAL PHARMACOLOGY

Amitriptyline hydrochloride is an antidepressant with sedative effects. Its mechanism of action in man is not known. It is not a monoamine oxidase inhibitor and it does not act primarily by stimulation of the central nervous system.

Amitriptyline inhibits the membrane pump mechanism responsible for uptake of norepinephrine and serotonin in adrenergic and serotonergic neurons. Pharmacologically, this action may potentiate or prolong neuronal activity since reuptake of these biogenic amines is important physiologically in terminating transmitting activity. This interference with reuptake of norepinephrine and/or serotonin is believed by some to underlie the antidepressant activity of amitriptyline.

INDICATIONS AND USAGE

For the relief of symptoms of depression. Endogenous depression is more likely to be alleviated than are other depressive states.

CONTRAINDICATIONS

Amitriptyline hydrochloride is contraindicated in patients who have shown prior hypersensitivity to it. It should not be given concomitantly with monoamine oxidase inhibitors. Hyperpyretic crises, severe convulsions, and deaths have occurred in patients receiving tricyclic antidepressant and monoamine oxidase inhibiting drugs simultaneously. When it is desired to replace a monoamine oxidase inhibitor with amitriptyline hydrochloride, a minimum of 14 days should be allowed to elapse after the former is discontinued. Amitriptyline hydrochloride should then be initiated cautiously with gradual increase in dosage until optimum response is achieved.

Amitriptyline hydrochloride should not be given with cisapride due to the potential for increased QT interval and increased risk for arrhythmia.

This drug is not recommended for use during the acute recovery phase following myocardial

Infarction.

WARNINGS

Clinical Worsening and Suicide Risk

Patients with major depressive disorder (MDD), both adult and pediatric, may experience worsening of their depression and/or the emergence of suicidal ideation and behavior (suicidality) or unusual changes in behavior, whether or not they are taking antidepressant medications, and this risk may persist until significant remission occurs. Suicide is a known risk of depression and certain other psychiatric disorders, and these disorders themselves are the strongest predictors of suicide. There has been a long-standing concern, however, that antidepressants may have a role in inducing worsening of depression and the emergence of suicidality in certain patients during the early phases of treatment. Pooled analyses of short-term placebo-controlled trials of antidepressant drugs (SSRIs and others) showed that these drugs increase the risk of suicidal thinking and behavior (suicidality) in children, adolescents, and young adults (ages 18 to 24) with major depressive disorder (MDD) and other psychiatric disorders. Short-term studies did not show an increase in the risk of suicidality with antidepressants compared to placebo in adults beyond age 24; there was a reduction with antidepressants compared to placebo in adults aged 65 and older.

The pooled analyses of placebo-controlled trials in children and adolescents with MDD, obsessive compulsive disorder (OCD), or other psychiatric disorders included a total of 24 short-term trials of 9 antidepressant drugs in over 4,400 patients. The pooled analyses of placebo-controlled trials in adults with MDD or other psychiatric disorders included a total of 295 short-term trials (median duration of 2 months) of 11 antidepressant drugs in over 77,000 patients. There was considerable variation in risk of suicidality among drugs, but a tendency toward an increase in the younger patients for almost all drugs studied. There were differences in absolute risk of suicidality across the different indications, with the highest incidence in MDD. The risk differences (drug vs. placebo), however, were relatively stable

within age strata and across indications. These risk differences (drug-placebo difference in the number of cases of suicidality per 1000 patients treated) are provided in Table 1.

Table 1
Age Range | Drug-Placebo Difference in Number of Cases of Suicidality per 1000 Patients Treated
 | Increases Compared to Placebo
<18 | 14 additional cases
18-24 | 5 additional cases
 | Decreases Compared to Placebo
25-64 | 1 fewer case
≥65 | 6 fewer cases

No suicides occurred in any of the pediatric trials. There were suicides in the adult trials, but the number was not sufficient to reach any conclusion about drug effect on suicide.

It is unknown whether the suicidality risk extends to longer-term use, i.e., beyond several months. However, there is substantial evidence from placebo-controlled maintenance trials in adults with depression that the use of antidepressants can delay the recurrence of depression.

All patients being treated with antidepressants for any indication should be monitored appropriately and observed closely for clinical worsening, suicidality, and unusual changes in behavior, especially during the initial few months of a course of drug therapy, or at times of dose changes, either increases or decreases.

The following symptoms, anxiety, agitation, panic attacks, insomnia, irritability, hostility,

aggressiveness, impulsivity, akathisia (psychomotor restlessness), hypomania, and mania, have been reported in adult and pediatric patients being treated with antidepressants for major depressive disorder as well as for other indications, both psychiatric and nonpsychiatric. Although a causal link between the emergence of such symptoms and either the worsening of depression and/or the emergence of suicidal impulses has not been established, there is concern that such symptoms may represent precursors to emerging suicidality.

Consideration should be given to changing the therapeutic regimen, including possibly discontinuing the medication, in patients whose depression is persistently worse, or who are experiencing emergent suicidality or symptoms that might be precursors to worsening depression or suicidality, especially if these symptoms are severe, abrupt in onset, or were not part of the patient's presenting symptoms.

Families and caregivers of patients being treated with antidepressants for major depressive disorder or other indications, both psychiatric and nonpsychiatric, should be alerted about the need to monitor patients for the emergence of agitation, irritability, unusual changes in behavior, and the other symptoms described above, as well as the emergence of suicidality, and to report such symptoms immediately to health care providers. Such monitoring should include daily observation by families and caregivers.

Prescriptions for amitriptyline hydrochloride tablets should be written for the smallest quantity of tablets consistent with good patient management, in order to reduce the risk of overdose.

Serotonin Syndrome

The development of a potentially life-threatening serotonin syndrome has been reported with tricyclic antidepressants, including Amitriptyline hydrochloride, alone but particularly with concomitant use of other serotonergic drugs (including triptans, tricyclic antidepressants, SSRI/SNRI, fentanyl, lithium, tramadol, tryptophan, buspirone, and St. John's Wort) and with drugs that impair metabolism of serotonin (in particular, MAOIs, both those intended to treat psychiatric disorders and also others, such as linezolid and intravenous methylene blue). Serotonin syndrome symptoms may include mental status changes (e.g., agitation, hallucinations, delirium, and coma), autonomic instability (e.g., tachycardia, labile blood pressure, dizziness, diaphoresis, flushing, hyperthermia), neuromuscular changes (e.g., tremor, rigidity, myoclonus, hyperreflexia, incoordination), seizures, and/or gastrointestinal symptoms (e.g., nausea, vomiting, diarrhea). Patients should be monitored for the emergence of serotonin syndrome.

The concomitant use of Amitriptyline hydrochloride with MAOIs intended to treat psychiatric disorders is contraindicated Amitriptyline hydrochloride should also not be started in a patient who is being treated with MAOIs such as linezolid or intravenous methylene blue. All reports with methylene blue that provided information on the route of administration involved intravenous administration in the dose range of 1 mg/kg to 8 mg/kg. No reports involved the administration of methylene blue by other routes (such as oral tablets or local tissue injection) or at lower doses. There may be circumstances when it is necessary to initiate treatment with an MAOI such as linezolid or intravenous methylene blue in a patient taking Amitriptyline hydrochloride. Amitriptyline hydrochloride should be discontinued before initiating treatment with the MAOI (see CONTRAINDICATIONS and DOSAGE AND ADMINISTRATION). If concomitant use of Amitriptyline hydrochloride with other serotonergic drugs, including triptans, tricyclic antidepressants, fentanyl, lithium, tramadol,

buspirone, tryptophan, and St. John's Wort is clinically warranted, patients should be made aware of a potential increased risk for serotonin syndrome, particularly during treatment initiation and dose increases. Treatment with Amitriptyline hydrochloride and any concomitant serotonergic agents should be discontinued immediately if the above events occur and supportive symptomatic treatment should be initiated.

Screening Patients for Bipolar Disorder

A major depressive episode may be the initial presentation of bipolar disorder. It is generally believed (though not established in controlled trials) that treating such an episode with an antidepressant alone may increase the likelihood of precipitation of a mixed/manic episode in patients at risk for bipolar disorder. Whether any of the symptoms described above represent such a conversion is unknown. However, prior to initiating treatment with an antidepressant, patients with depressive symptoms should be adequately screened to determine if they are at risk for bipolar disorder; such screening should include a detailed psychiatric history, including a family history of suicide, bipolar disorder, and depression. It should be noted that amitriptyline hydrochloride is not approved for use in treating bipolar depression.

Amitriptyline hydrochloride may block the antihypertensive action of guanethidine or similarly acting compounds.

It should be used with caution in patients with a history of seizures and, because of its atropine-like action, in patients with a history of urinary retention or angle-closure glaucoma. In patients with angle closure glaucoma, even average doses may precipitate an attack.

Patients with cardiovascular disorders should be watched closely. Tricyclic antidepressant drugs, including amitriptyline hydrochloride, particularly when given in high doses, have been reported to produce arrhythmias, sinus tachycardia, and prolongation of the conduction time. Myocardial infarction and stroke have been reported with drugs of this class.

Close supervision is required when amitriptyline hydrochloride is given to hyperthyroid patients or those receiving thyroid medication.

Amitriptyline hydrochloride may enhance the response to alcohol and the effects of barbiturates and other CNS depressants. In patients who may use alcohol excessively, it should be borne in mind that the potentiation may increase the danger inherent in any suicide attempt or overdosage. Delirium has been reported with concurrent administration of amitriptyline and disulfiram.

Hyponatremia

Hyponatremia has occurred as a result of treatment with Amitriptyline hydrochloride tablets. In many cases, hyponatremia appears to be the result of the syndrome of inappropriate antidiuretic hormone secretion (SIADH). Signs and symptoms of hyponatremia include headache, difficulty concentrating, memory impairment, confusion, weakness, and unsteadiness, which may lead to falls. Signs and symptoms associated with more severe and/or acute cases have included syncope, seizure, coma, respiratory arrest, and death.

In patients with symptomatic hyponatremia, discontinue Amitriptyline hydrochloride tablets and institute appropriate medical intervention. Elderly patients, patients taking diuretics, and those who are volume-depleted may be at greater risk of developing hyponatremia with Amitriptyline hydrochloride tablets.

Angle-Closure Glaucoma

The pupillary dilation that occurs following use of many antidepressant drugs including amitriptyline hydrochloride may trigger an angle closure attack in a patient with anatomically narrow angles who does not have a patent iridectomy.

Usage in Pregnancy

Teratogenic effects were not observed in mice, rats, or rabbits when amitriptyline was given orally at doses of 2 to 40 mg/kg/day (up to 13 times the maximum recommended human dose^1). Studies in literature have shown amitriptyline to be teratogenic in mice and hamsters when given by various routes of administration at doses of 28 to 100 mg/kg/day (9 to 33 times the maximum recommended human dose), producing multiple malformations. Another study in the rat reported that an oral dose of 25 mg/kg/day (8 times the maximum recommended human dose) produced delays in ossification of fetal vertebral bodies without other signs of embryotoxicity. In rabbits, an oral dose of 60 mg/kg/day (20 times the maximum recommended human dose) was reported to cause incomplete ossification of cranial bones.

Amitriptyline has been shown to cross the placenta. Although a causal relationship has not been established, there have been a few reports of adverse events, including CNS effects, limb deformities, or developmental delay, in infants whose mothers had taken amitriptyline during pregnancy.

There are no adequate and well-controlled studies in pregnant women. Amitriptyline hydrochloride should be used during pregnancy only if the potential benefit to the mother justifies the potential risk to the fetus.

^1Based on a maximum recommended amitriptyline dose of 150 mg/day or 3 mg/kg/day for a 50 kg patient.

Nursing Mothers

Amitriptyline is excreted into breast milk. In one report in which a patient received amitriptyline 100 mg/day while nursing her infant, levels of 83 to 141 ng/mL were detected in the mother's serum. Levels of 135 to 151 ng/mL were found in the breast milk, but no trace of the drug could be detected in the infant's serum.

Because of the potential for serious adverse reactions in nursing infants from amitriptyline, a decision should be made whether to discontinue nursing or to discontinue the drug, taking into account the importance of the drug to the mother.

Usage in Pediatric Patients

In view of the lack of experience with the use of this drug in pediatric patients, it is not recommended at the present time for patients under 12 years of age.

PRECAUTIONS

Schizophrenic patients may develop increased symptoms of psychosis; patients with paranoid

symptomatology may have an exaggeration of such symptoms. Depressed patients, particularly those with known manic-depressive illness, may experience a shift to mania or hypomania. In these circumstances the dose of amitriptyline may be reduced or a major tranquilizer such as perphenazine may be administered concurrently.

The possibility of suicide in depressed patients remains until significant remission occurs. Potentially suicidal patients should not have access to large quantities of this drug. Prescriptions should be written for the smallest amount feasible.

Concurrent administration of amitriptyline hydrochloride and electroshock therapy may increase the hazards associated with such therapy. Such treatment should be limited to patients for whom it is essential.

When possible, the drug should be discontinued several days before elective surgery.

Both elevation and lowering of blood sugar levels have been reported.

Amitriptyline hydrochloride should be used with caution in patients with impaired liver function.

Information for Patients

Prescribers or other health professionals should inform patients, their families, and their caregivers about the benefits and risks associated with treatment with amitriptyline hydrochloride tablets and should counsel them in its appropriate use. A patient Medication Guide about "Antidepressant Medicines, Depression and other Serious Mental Illnesses, and Suicidal Thoughts or Actions" is available for amitriptyline hydrochloride tablets. The prescriber or health professional should instruct patients, their families, and their caregivers to read the Medication Guide and should assist them in understanding its contents. Patients should be given the opportunity to discuss the contents of the Medication Guide and to obtain answers to any questions they may have. The complete text of the Medication Guide is reprinted at the end of this document.

Patients should be advised of the following issues and asked to alert their prescriber if these occur while taking amitriptyline hydrochloride tablets.

Patients should be advised that taking amitriptyline hydrochloride tablets can cause mild pupillary dilation, which in susceptible individuals, can lead to an episode of angle-closure glaucoma. Pre-existing glaucoma is almost always open-angle glaucoma because angle-closure glaucoma, when diagnosed, can be treated definitively with iridectomy. Open-angle glaucoma is not a risk factor for angle-closure glaucoma. Patients may wish to be examined to determine whether they are susceptible to angle closure, and have a prophylactic procedure (e.g., iridectomy), if they are susceptible.

Clinical Worsening and Suicide Risk

Patients, their families, and their caregivers should be encouraged to be alert to the emergence of anxiety, agitation, panic attacks, insomnia, irritability, hostility, aggressiveness, impulsivity, akathisia (psychomotor restlessness), hypomania, mania, other unusual changes in behavior, worsening of depression, and suicidal ideation, especially early during antidepressant treatment and when the dose is adjusted up or down. Families and caregivers of patients should be advised to look for the emergence of such symptoms on a day-to-day basis, since changes may be abrupt. Such symptoms should be reported to the patient's prescriber or health professional, especially if they are severe, abrupt in onset, or were not part of the patient's presenting symptoms. Symptoms such as these may be associated with an increased risk for suicidal thinking and behavior and indicate a need for very close monitoring and possibly changes in the medication.

While on therapy with amitriptyline hydrochloride, patients should be advised as to the possible impairment of mental and/or physical abilities required for performance of hazardous tasks, such as operating machinery or driving a motor vehicle.

Drug Interactions

Topiramate

Some patients may experience a large increase in amitriptyline concentration in the presence of topiramate and any adjustments in amitriptyline dose should be made according to the patient's clinical response and not on the basis of plasma levels.

Drugs Metabolized by P450 2D6

The biochemical activity of the drug metabolizing isozyme cytochrome P450 2D6 (debrisoquin hydroxylase) is reduced in a subset of the caucasian population (about 7 to 10% of Caucasians are so called "poor metabolizers"); reliable estimates of the prevalence of reduced P450 2D6 isozyme activity among Asian, African and other populations are not yet available. Poor metabolizers have higher than expected plasma concentrations of tricyclic antidepressants (TCAs) when given usual doses. Depending on the fraction of drug metabolized by P450 2D6, the increase in plasma concentration may be small, or quite large (8 fold increase in plasma AUC of the TCA).

In addition, certain drugs inhibit the activity of this isozyme and make normal metabolizers resemble poor metabolizers. An individual who is stable on a given dose of TCA may become abruptly toxic when given one of these inhibiting drugs as concomitant therapy. The drugs that inhibit cytochrome P450 2D6 include some that are not metabolized by the enzyme (quinidine; cimetidine) and many that are substrates for P450 2D6 (many other antidepressants, phenothiazines, and the Type 1C antiarrhythmics propafenone and flecainide). While all the selective serotonin reuptake inhibitors (SSRIs), e.g.,fluoxetine, sertraline, and paroxetine, inhibit P450 2D6, they may vary in the extent of inhibition. The extent to which SSRI-TCA interactions may pose clinical problems will depend on the degree of inhibition and the pharmacokinetics of the SSRI involved. Nevertheless, caution is indicated in the coadministration of TCAs with any of the SSRIs and also in switching from one class to the other. Of particular importance, sufficient time must elapse before initiating TCA treatment in a patient being withdrawn from fluoxetine, given the long half-life of the parent and active metabolite (at least 5 weeks may be necessary).

Concomitant use of tricyclic antidepressants with drugs that can inhibit cytochrome P450 2D6 may require lower doses than usually prescribed for either the tricyclic antidepressant or the other drug. Furthermore, whenever one of these other drugs is withdrawn from co-therapy, an increased dose of tricyclic antidepressant may be required. It is desirable to monitor TCA plasma levels whenever a TCA is going to be coadministered with another drug known to be an inhibitor of P450 2D6.

Monoamine oxidase inhibitors – see CONTRAINDICATIONSsection. Guanethidine or similarly acting compounds; thyroid medication; alcohol, barbiturates and other CNS depressants; and disulfiram – see WARNINGSsection.

When amitriptyline hydrochloride is given with anticholinergic agents or sympathomimetic drugs, including epinephrine combined with local anesthetics, close supervision and careful adjustment of dosages are required.

Hyperpyrexia has been reported when amitriptyline hydrochloride is administered with anticholinergic agents or with neuroleptic drugs, particularly during hot weather.

Paralytic ileus may occur in patients taking tricyclic antidepressants in combination with anticholinergic type drugs.

Cimetidine is reported to reduce hepatic metabolism of certain tricyclic antidepressants, thereby delaying elimination and increasing steady-state concentrations of these drugs. Clinically significant effects have been reported with the tricyclic antidepressants when used concomitantly with cimetidine. Increases in plasma levels of tricyclic antidepressants, and in the frequency and severity of side effects, particularly anticholinergic, have been reported when cimetidine was added to the drug regimen. Discontinuation of cimetidine in well-controlled patients receiving tricyclic antidepressants and cimetidine may decrease the plasma levels and efficacy of the antidepressants.

Caution is advised if patients receive large doses of ethchlorvynol concurrently. Transient delirium has been reported in patients who were treated with one gram of ethchlorvynol and 75 to 150 mg of amitriptyline hydrochloride.

Geriatric Use

Clinical experience has not identified differences in responses between elderly and younger patients. In general, dose selection for an elderly patient should be cautious, usually starting at the low end of the dosing range, reflecting the greater frequency of decreased hepatic function, concomitant disease and other drug therapy in elderly patients.

Geriatric patients are particularly sensitive to the anticholinergic side effects of tricyclic antidepressants including amitriptyline hydrochloride. Peripheral anticholinergic effects include tachycardia, urinary retention, constipation, dry mouth, blurred vision, and exacerbation of narrow-angle glaucoma. Central nervous system anticholinergic effects include cognitive impairment, psychomotor slowing, confusion, sedation, and delirium. Elderly patients taking amitriptyline hydrochloride may be at increased risk for falls. Elderly patients should be started on low doses of amitriptyline hydrochloride and observed closely (see DOSAGE AND ADMINISTRATION).

Pediatric Use

Safety and effectiveness in the pediatric population have not been established (see BOX WARNINGand WARNINGS: Clinical Worsening and Suicide Risk). Anyone considering the use of amitriptyline in a child or adolescent must balance the potential risks with the clinical need.

ADVERSE REACTIONS

Within each category the following adverse reactions are listed in order of decreasing severity. Included in the listing are a few adverse reactions which have not been reported with this specific drug. However, pharmacological similarities among the tricyclic antidepressant drugs require that each of the reactions be considered when amitriptyline is administered.

Cardiovascular

Myocardial infarction; stroke; nonspecific ECG changes and changes in AV conduction; heart block; arrhythmias; hypotension, particularly orthostatic hypotension; syncope; hypertension; tachycardia; palpitation.

CNS and Neuromuscular

Coma; seizures; hallucinations; delusions; confusional states; disorientation; incoordination; ataxia; tremors; peripheral neuropathy; numbness, tingling and paresthesias of the extremities; extrapyramidal symptoms including abnormal involuntary movements and tardive dyskinesia; dysarthria; disturbed concentration; excitement; anxiety; insomnia; restlessness; nightmares; drowsiness; dizziness; weakness; fatigue; headache; syndrome of inappropriate ADH (antidiuretic hormone) secretion; tinnitus; alteration in EEG patterns.

Anticholinergic

Paralytic ileus, hyperpyrexia; urinary retention, dilatation of the urinary tract; constipation; blurred vision, disturbance of accommodation, increased ocular pressure, mydriasis; dry mouth.

Allergic

Skin rash; urticaria; photosensitization; edema of face and tongue.

Hematologic

Bone marrow depression including agranulocytosis, leukopenia, thrombocytopenia; purpura;

eosinophilia.

Gastrointestinal

Rarely hepatitis (including altered liver function and jaundice); nausea; epigastric distress; vomiting; anorexia; stomatitis; peculiar taste; diarrhea; parotid swelling; black tongue.

Endocrine

Testicular swelling and gynecomastia in the male; breast enlargement and galactorrhea in the female; increased or decreased libido; impotence; elevation and lowering of blood sugar levels.

Other

Alopecia; edema; weight gain or loss; urinary frequency; increased perspiration; hyponatremia.

Withdrawal Symptoms

After prolonged administration, abrupt cessation of treatment may produce nausea, headache, and malaise. Gradual dosage reduction has been reported to produce, within two weeks, transient symptoms including irritability, restlessness, and dream and sleep disturbance.

These symptoms are not indicative of addiction. Rare instances have been reported of mania or hypomania occurring within 2 to 7 days following cessation of chronic therapy with tricyclic antidepressants.

Causal Relationship Unknown

Other reactions, reported under circumstances where a causal relationship could not be established, are listed to serve as alerting information to physicians:

Body as a Whole

Lupus-like syndrome (migratory arthritis, positive ANA and rheumatoid factor).

Digestive

Hepatic failure, ageusia.

Post marketing Adverse Events

A syndrome resembling neuroleptic malignant syndrome (NMS) has been very rarely reported after starting or increasing the dose of amitriptyline hydrochloride, with and without concomitant medications known to cause NMS. Symptoms have included muscle rigidity, fever, mental status changes, diaphoresis, tachycardia, and tremor.

Very rare cases of serotonin syndrome (SS) have been reported with amitriptyline hydrochloride in combination with other drugs that have a recognized association with SS.

To report SUSPECTED ADVERSE REACTIONS, contact Unichem Pharmaceuticals (USA) Inc.at 1-866-562-4616 or FDA at 1 800-FDA-1088 or www.fda.gov/medwatch.

OVERDOSAGE

Deaths may occur from overdosage with this class of drugs. Multiple drug ingestion (including alcohol) is common in deliberate tricyclic antidepressant overdose. As the management is complex and changing, it is recommended that the physician contact a poison control center for current information on treatment. Signs and symptoms of toxicity develop rapidly after tricyclic antidepressant overdose, therefore, hospital monitoring is required as soon as possible.

Manifestations

Critical manifestations of overdose include: cardiac dysrhythmias, severe hypotension, convulsions, and CNS depression, including coma. Changes in the electrocardiogram particularly in QRS axis or width, are clinically significant indicators of tricyclic antidepressant toxicity. In addition, a rightward axis shift in the terminal QRS complex together with a prolonged QT interval and sinus tachycardia are specific and sensitive indicators of first generation tricyclic overdose. The absence of these findings is not exclusionary. Prolonged PR interval, ST-T wave changes, ventricular tachycardia and fibrillation may also occur.

Other signs of overdose may include: impaired myocardial contractility, confusion, disturbed

concentration, transient visual hallucinations, dilated pupils, disorders of ocular motility, agitation, hyperactive reflexes polyradiculoneuropathy, stupor, drowsiness, muscle rigidity, vomiting, hypothermia, hyperpyrexia, or any of the symptoms listed under ADVERSE REACTIONS.

Management

General

Obtain an ECG and immediately initiate cardiac monitoring. Protect the patient's airway, establish an intravenous line and initiate gastric decontamination. A minimum of six hours of observation with cardiac monitoring and observation for signs of CNS or respiratory depression, hypotension, cardiac dysrhythmias and/or conduction blocks, and seizures is necessary. If signs of toxicity occur at any time during the period, extended monitoring is required. There are case reports of patients succumbing to fatal dysrhythmias late after overdose; these patients had clinical evidence of significant poisoning prior to death and most received inadequate gastrointestinal decontamination. Monitoring of plasma drug levels should not guide management of the patient.

Gastrointestinal Decontamination

All patients suspected of tricyclic antidepressant overdose should receive gastrointestinal

decontamination. This should include, large volume gastric lavage followed by activated charcoal. If consciousness is impaired, the airway should be secured prior to lavage. EMESIS IS CONTRAINDICATED.

Cardiovascular

A maximal limb-lead QRS duration of ≥0.10 seconds may be the best indication of the severity of the overdose. Intravenous sodium bicarbonate should be used to maintain the serum pH in the range of 7.45 to 7.55. If the pH response is inadequate, hyperventilation may also be used. Concomitant use of hyperventilation and sodium bicarbonate should be done with extreme caution, with frequent pH monitoring. A pH >7.60 or a pCO2<20 mm Hg is undesirable. Dysrhythmias unresponsive to sodium bicarbonate therapy/hyperventilation may respond to lidocaine, bretylium or phenytoin. Type 1A and 1C antiarrhythmics are generally contraindicated (e.g., quinidine, disopyramide, and procainamide).

In rare instances, hemoperfusion may be beneficial in acute refractory cardiovascular instability in patients with acute toxicity. However, hemodialysis, peritoneal dialysis, exchange transfusions, and forced diuresis generally have been reported as ineffective in tricyclic antidepressant poisoning.

CNS

In patients with CNS depression early intubation is advised because of the potential for abrupt deterioration. Seizures should be controlled with benzodiazepines, or if these are ineffective, other anticonvulsants (e.g., phenobarbital, phenytoin).

Physostigmine is not recommended except to treat life-threatening symptoms that have been unresponsive to other therapies, and then only in consultation with a poison control center.

Psychiatric Follow-up

Since overdosage is often deliberate, patients may attempt suicide by other means during the recovery phase. Psychiatric referral may be appropriate.

Pediatric Management

The principles of management of pediatric and adult overdosages are similar. It is strongly

recommended that the physician contact the local poison control center for specific pediatric treatment.

DOSAGE AND ADMINISTRATION

Oral Dosage

Dosage should be initiated at a low level and increased gradually, noting carefully the clinical response and any evidence of intolerance.

Initial Dosage for Adults

For outpatients, 75 mg of amitriptyline hydrochloride a day in divided doses is usually satisfactory. If necessary, this may be increased to a total of 150 mg per day. Increases are made preferably in the late afternoon and/or bedtime doses. A sedative effect may be apparent before the antidepressant effect is noted, but an adequate therapeutic effect may take as long as 30 days to develop.

An alternate method of initiating therapy in outpatients is to begin with 50 to 100 mg amitriptyline hydrochloride at bedtime. This may be increased by 25 or 50 mg as necessary in the bedtime dose to a total of 150 mg per day.

Hospitalized patients may require 100 mg a day initially. This can be increased gradually to 200 mg a day if necessary. A small number of hospitalized patients may need as much as 300 mg a day.

Adolescent and Elderly Patients

In general, lower dosages are recommended for these patients. Ten mg 3 times a day with 20 mg at bedtime may be satisfactory in adolescent and elderly patients who do not tolerate higher dosages.

Maintenance

The usual maintenance dosage of amitriptyline hydrochloride is 50 to 100 mg per day. In some patients, 40 mg per day is sufficient. For maintenance therapy, the total daily dosage may be given in a single dose, preferably at bedtime. When satisfactory improvement has been reached, dosage should be reduced to the lowest amount that will maintain relief of symptoms. It is appropriate to continue maintenance therapy 3 months or longer to lessen the possibility of relapse.

Usage in Pediatric Patients

In view of the lack of experience with the use of this drug in pediatric patients, it is not recommended at the present time for patients under 12 years of age.

Plasma Levels

Because of the wide variation in the absorption and distribution of tricyclic antidepressants in body fluids, it is difficult to directly correlate plasma levels and therapeutic effect. However, determination of plasma levels may be useful in identifying patients who appear to have toxic effects and may have excessively high levels, or those in whom lack of absorption or noncompliance is suspected. Because of increased intestinal transit time and decreased hepatic metabolism in elderly patients, plasma levels are generally higher for a given oral dose of amitriptyline hydrochloride than in younger patients.

Elderly patients should be monitored carefully and quantitative serum levels obtained as clinically appropriate. Adjustments in dosage should be made according to the patient's clinical response and not on the basis of plasma levels.^2

^2Hollister, L.E.; Monitoring Tricyclic Antidepressant Plasma Concentrations. JAMA 1979; 241(23):2530-2533.

HOW SUPPLIED

Amitriptyline hydrochloride tablets, USP for oral administration are available as:

25 mg: Yellow colored, round shaped, film-coated tablets, debossed with "420" on one side and "U" on the other side, and supplied as:

NDC 72789-305-30 bottles of 30

Store at 20º to 25ºC (68º to 77ºF); excursions permitted to 15° to 30°C (59° to 86°F) [See USP Controlled Room Temperature].

Dispense in a tight, light-resistant container.

KEEP OUT OF THE REACH OF CHILDREN.

METABOLISM

Studies in man following oral administration of^14C-labeled drug indicated that amitriptyline is rapidly absorbed and metabolized. Radioactivity of the plasma was practically negligible, although significant amounts of radioactivity appeared in the urine by 4 to 6 hours and one-half to one-third of the drug was excreted within 24 hours.

Amitriptyline is metabolized by N-demethylation and bridge hydroxylation in man, rabbit, and rat. Virtually the entire dose is excreted as glucuronide or sulfate conjugate of metabolites, with little unchanged drug appearing in the urine. Other metabolic pathways may be involved.

REFERENCES

Ayd FJ Jr: Amitriptyline therapy for depressive reactions. Psychosomatics 1960;1:320-325.

Diamond S: Human metabolizer of amitriptyline tagged with carbon 14.Curr Ther Res, Mar 1965, pp170-175.

Dorfman W: Clinical experiences with amitriptyline: A preliminary report. Psychosomatics 1960;1:153- 155.

Fallette JM, Stasney CR, Mintz AA: Amitriptyline poisoning treated with physostigmine. South MedJ 1970;63:1492-1493.

Hollister LE, Overall JE, Johnson M, et al: Controlled comparison of amitriptyline, imipramine and placebo in hospitalized depressed patients. J Nerv Ment Dis 1964;139:370-375.

Hordern A, Burt CG, Holt NF: Depressive states: A pharmacotherapeutic study, Springfield study. Springfield, Ill, Charles C. Thomas, 1965.

Jenike MA: Treatment of Affective Illness in the Elderly with Drugs and Electroconvulsive Therapy. J Geriatr Psychiatry 1989;22(1):77-112.

Klerman GL, Cole JO: Clinical pharmacology of imipramine and related antidepressant compounds. Int J Psychiatry 1976;3:267-304.

Liu B, Anderson G, Mittman N, et al: Use of selective serotonin-reuptake inhibitors or tricyclic antidepressants and risk of hip fractures in elderly people. Lancet 1998;351 (9112):1303-1307.

McConaghy N, Joffe AD, Kingston WA, et al: Correlation of clinical features of depressed outpatients with response to amitriptyline and protriptyline. Br J Psychiatry 1968;114:103-106.

McDonald IM, Perkins M, Marjerrison G, et al: A controlled comparison of amitriptyline and electroconvulsive therapy in the treatment of depression. Am J Psychiatry 1966;122:1427-1431.

Slovis T, Ott J, Teitelbaum D, et al: Physostigmine therapy in acute tricyclic antidepressant poisoning.Clin Toxicol 1971;4:451-459.

Symposium on depression with special studies of a new antidepressant, amitriptyline. Dis Nerv Syst,(Sect 2) May 1961, pp 5-56.

04-R-06/2025

13016326

MEDICATION GUIDE

Amitriptyline Hydrochloride Tablets , USP

(a-mee-TRIP-ti-leen)

Antidepressant Medicines , Depression and other Serious Mental Illnesses , and Suicidal Thoughts or Actions

Read the Medication Guide that comes with you or your family member's antidepressant medicine. This Medication Guide is only about the risk of suicidal thoughts and actions with antidepressant medicines.

Talk to your, or your family member's , healthcare provider about:

- all risks and benefits of treatment with antidepressant medicines
- all treatment choices for depression or other serious mental illness

What is the most important information I should know about antidepressant medicines,

depression and other serious mental illnesses , and suicidal thoughts or actions

1. Antidepressant medicines may increase suicidal thoughts or actions in some children, teenagers, and young adults within the first few months of treatment.

2. Depression and other serious mental illnesses are the most important causes of

Suicidal thoughts and actions. Some people may have a particularly high risk of having suicidal thoughts or actions.These include people who have (or have a family history of) bipolar illness (also called manic-depressive illness) or suicidal thoughts or actions.

3. How can I watch for and try to prevent suicidal thoughts and actions in myself or a family member?

- Pay close attention to any changes, especially sudden changes, in mood, behaviors, thoughts, or feelings. This is very important when an antidepressant medicine is started or when the dose is changed.
- Call the healthcare provider right away to report new or sudden changes in mood, behavior, thoughts, or feelings.
- Keep all follow-up visits with the healthcare provider as scheduled. Call the healthcare provider between visits as needed, especially if you have concerns about symptoms.

Call a healthcare provider right away if you or your family member has any of the following symptoms, especially if they are new, worse, or worry you:

- Serotonin Syndrome. This condition can be life-threatening and symptoms may include:
  - agitation, hallucinations, coma, or other changes in mental status
  - racing heartbeat, high or low blood pressure
  - coordination problems or muscle twitching (overactive reflexes)
  - nausea, vomiting, or diarrhea
  - sweating or fever
  - muscle rigidity
- thoughts about suicide or dying
- attempts to commit suicide
- new or worse depression
- new or worse anxiety
- feeling very agitated or restless
- panic attacks
- trouble sleeping (insomnia)
- new or worse irritability
- acting aggressive, being angry, or violent
- acting on dangerous impulses
- an extreme increase in activity and talking (mania)
- other unusual changes in behavior or mood
- Low salt (Sodium) levels in the blood. Elderly people may be at greater risk for this. Symptoms may include:
  - Headache
  - Weakness or feeling unsteady
  - Confusion, problems concentrating or thinking or memory problems.
- Visual problems :eye pain, changes in vision, swelling or redness in or around the eye

What else do I need to know about antidepressant medicines?

- Never stop an antidepressant medicine without first talking to a healthcare provider.

Stopping an antidepressant medicine suddenly can cause other symptoms.

- Visual problems.Only some people are at risk for these problems. You may want to undergo an eye examination to see if you are at risk and receive preventative treatment if you are.
- Antidepressants are medicines used to treat depression and other illnesses.It is important to discuss all the risks of treating depression and also the risks of not treating it. Patients and their families or other caregivers should discuss all treatment choices with the healthcare provider, not just the use of antidepressants.
- Antidepressant medicines have other side effects.Talk to the healthcare provider about the side effects of the medicine prescribed for you or your family member.
- Antidepressant medicines can interact with other medicines.Know all of the medicines that you or your family member takes. Keep a list of all medicines to show the healthcare provider. Do not start new medicines without first checking with your healthcare provider.
- Not all antidepressant medicines prescribed for children are FDA approved for use in children.Talk to your child's healthcare provider for more information.
- Tell your healthcare provider if you have low sodium levels in your blood during treatment with Amitriptyline hydrochloride tablets.

Call your doctor for medical advice about side effects . You may report side effects to FDA at 1- 800-FDA-1088.

This Medication Guide has been approved by the U.S. Food and Drug Administration for all antidepressants.

Additional medication guides can be obtained by calling Unichem at 1-866- 562-4616.

Rx only

UNICHEM LABORATORIES LTD.

Pilerne Ind. Estate, Pilerne, Bardez, Goa-403 511, India.

Manufactured for:

East Brunswick, NJ 08816

04-R-06/2025

13016326